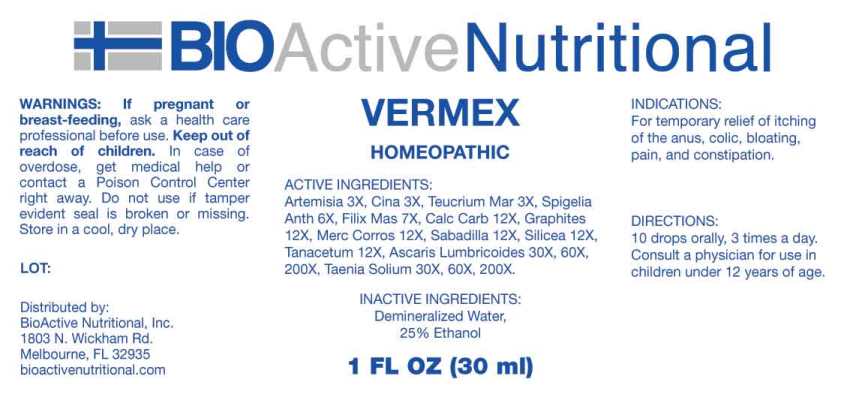 DRUG LABEL: Vermex
NDC: 43857-0606 | Form: LIQUID
Manufacturer: BioActive Nutritional, Inc.
Category: homeopathic | Type: HUMAN OTC DRUG LABEL
Date: 20250516

ACTIVE INGREDIENTS: ARTEMISIA VULGARIS ROOT 3 [hp_X]/1 mL; ARTEMISIA CINA PRE-FLOWERING TOP 3 [hp_X]/1 mL; TEUCRIUM MARUM WHOLE 3 [hp_X]/1 mL; SPIGELIA ANTHELMIA WHOLE 6 [hp_X]/1 mL; DRYOPTERIS FILIX-MAS ROOT 7 [hp_X]/1 mL; OYSTER SHELL CALCIUM CARBONATE, CRUDE 12 [hp_X]/1 mL; GRAPHITE 12 [hp_X]/1 mL; MERCURIC CHLORIDE 12 [hp_X]/1 mL; SCHOENOCAULON OFFICINALE SEED 12 [hp_X]/1 mL; SILICON DIOXIDE 12 [hp_X]/1 mL; TANACETUM VULGARE TOP 12 [hp_X]/1 mL; ASCARIS LUMBRICOIDES 30 [hp_X]/1 mL; TAENIA SOLIUM 30 [hp_X]/1 mL
INACTIVE INGREDIENTS: WATER; ALCOHOL

DRUG FACTS:

ACTIVE INGREDIENTS:

Artemisia Vulgaris 3X, Cina 3X, Teucrium Marum 3X, Spigelia Anthelmia 6X, Filix Mas 7X, Calcarea Carbonica 12X, Graphites 12X, Mercurius Corrosivus 12X, Sabadilla 12X, Silicea 12X, Tanacetum Vulgare 12X, Ascaris Lumbricoides 30X, 60X, 200X, Taenia Solium 30X, 60X, 200X.

INDICATIONS:

For temporary relief of itching of the anus, colic, bloating, pain, and constipation.

WARNINGS:

If pregnant or breast-feeding, ask a health care professional before use.

Keep out of reach of children. In case of overdose, get medical help or contact a Poison Control Center right away.

Do not use if tamper evident seal is broken or missing.

Store in a cool, dry place.

Keep out of reach of children. In case of overdose, get medical help or contact a Poison Control Center right away.

DIRECTIONS:

10 drops orally, 3 times a day. Consult a physician for use in children under 12 years of age.

INDICATIONS:

For temporary relief of itching of the anus, colic, bloating, pain, and constipation.

INACTIVE INGREDIENTS:

Demineralized Water, 25% Ethanol

QUESTIONS:

Distributed by:
BioActive Nutritional, Inc.
1803 N. Wickham Rd.
Melbourne, FL 32935
bioactivenutritional.com

PACKAGE LABEL DISPLAY:

BIOActive Nutritional

VERMEX

HOMEOPATHIC

1 FL OZ (30 ml)